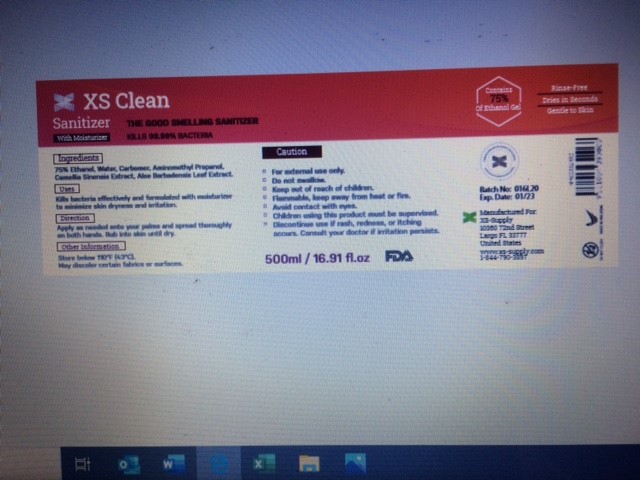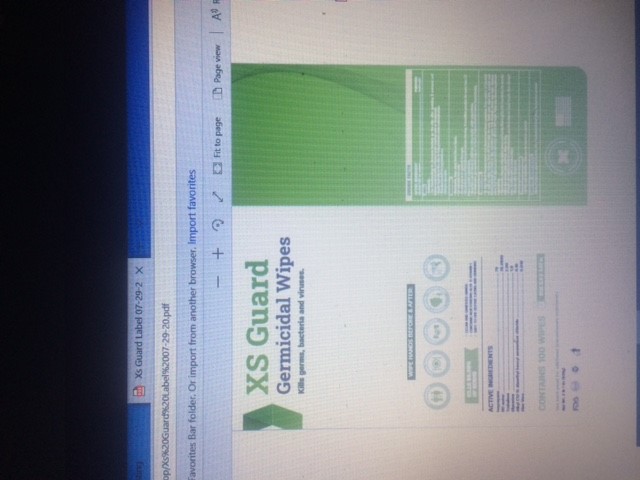 DRUG LABEL: XS Guard
NDC: 80015-112 | Form: LIQUID
Manufacturer: XS Supply LLC
Category: otc | Type: HUMAN OTC DRUG LABEL
Date: 20200806

ACTIVE INGREDIENTS: ISOPROPYL ALCOHOL 70 mL/100 mL
INACTIVE INGREDIENTS: WATER 30 mL/100 mL

XS Guard and XS Clean - Hand Sanitizer

use as needed

Warning - Keep out of the reach of children

Keep out of the reach of children

inactive ingredients

water

indications for use

Use if soap & water are noty available

keep out of the reach of children

active ingredient Isoproanol and active ingredient ethanol

Isopropyl at 70%, Ethanol at 75%

Purpose is hand sanitization

Package Labels Display Panel

see attached label copies